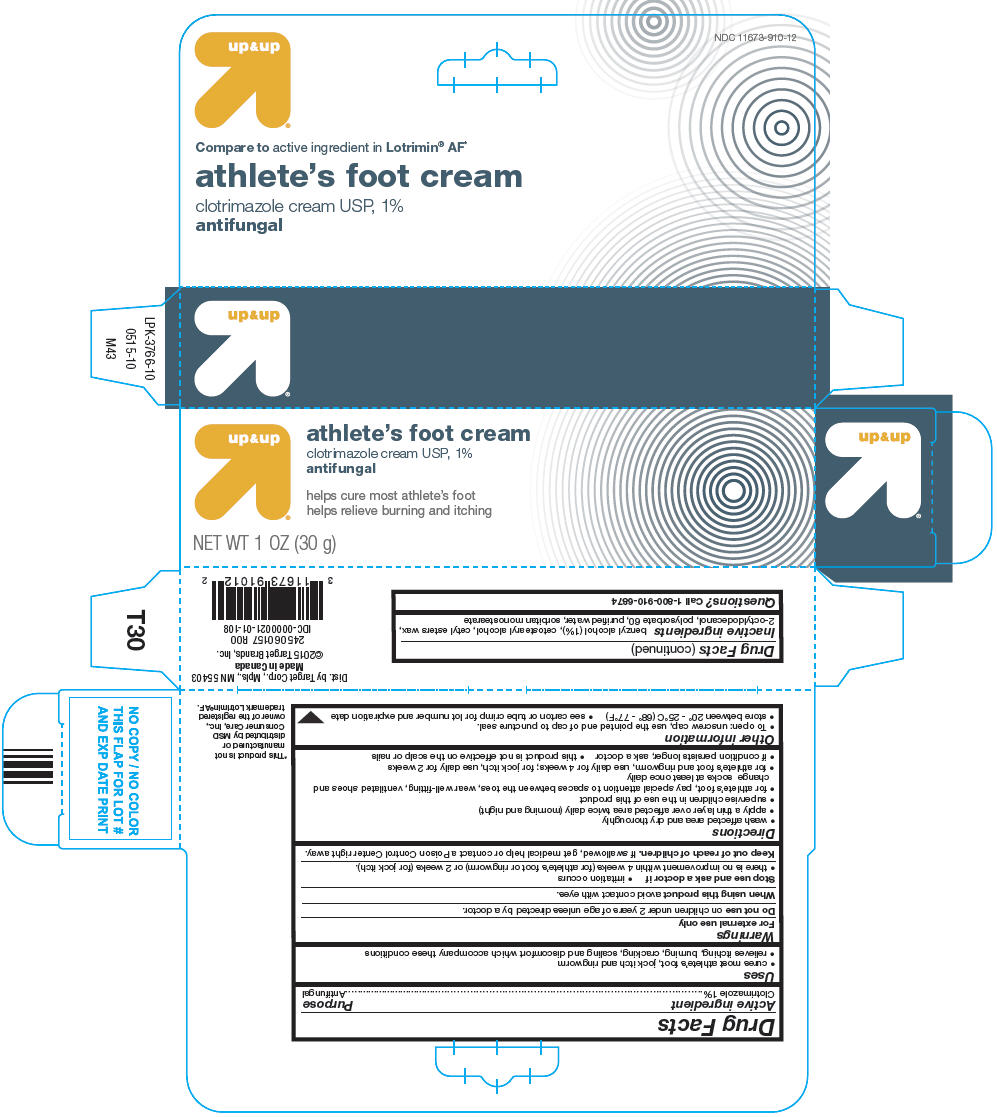 DRUG LABEL: UpandUp

NDC: 11673-910 | Form: CREAM
Manufacturer: Target Corporation
Category: otc | Type: HUMAN OTC DRUG LABEL
Date: 20250716

ACTIVE INGREDIENTS: CLOTRIMAZOLE 10 mg/1 g
INACTIVE INGREDIENTS: BENZYL ALCOHOL; CETOSTEARYL ALCOHOL; CETYL ESTERS WAX; OCTYLDODECANOL; POLYSORBATE 60; WATER; SORBITAN MONOSTEARATE

Up&Up
Clotrimazole 1%

Drug Facts

Active ingredient

Clotrimazole 1%

Purpose

Antifungal

Uses

- cures most athlete's foot, jock itch and ringworm
- relieves itching, burning, cracking, scaling and discomfort which accompany these conditions

Warnings

For external use only

DO NOT USE

Do not useon children under 2 years of age unless directed by a doctor.

When using this productavoid contact with eyes.

Stop use and ask a doctor if

- irritation occurs
- there is no improvement within 4 weeks (for athlete's foot or ringworm) or 2 weeks (for jock itch).

Keep out of reach of children.If swallowed, get medical help or contact a Poison Control Center right away.

Directions

- wash affected area and dry thoroughly
- apply a thin layer over affected area twice daily (morning and night)
- supervise children in the use of this product
- for athlete's foot, pay special attention to spaces between the toes, wear well-fitting, ventilated shoes and change socks at least once daily
- for athlete's foot and ringworm, use daily for 4 weeks; for jock itch, use daily for 2 weeks
- if condition persists longer, ask a doctor
- this product is not effective on the scalp or nails

Other information

- To open: unscrew cap, use the pointed end of cap to puncture seal.
- store between 20° - 25°C (68° - 77°F)
- see carton or tube crimp for lot number and expiration date

Inactive ingredients

benzyl alcohol (1%), cetostearyl alcohol, cetyl esters wax, 2-octyldodecanol, polysorbate 60, purified water, sorbitan monostearate

Questions?

Call 1-800-910-6874

Dist. by Target Corp., Mpls., MN 55403

PRINCIPAL DISPLAY PANEL - 30 g Tube Carton

up&up

athlete's foot cream
clotrimazole cream USP, 1%
antifungal

helps cure most athlete's foot
helps relieve burning and itching

NET WT 1 OZ (30 g)